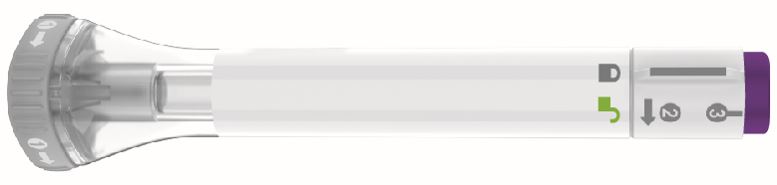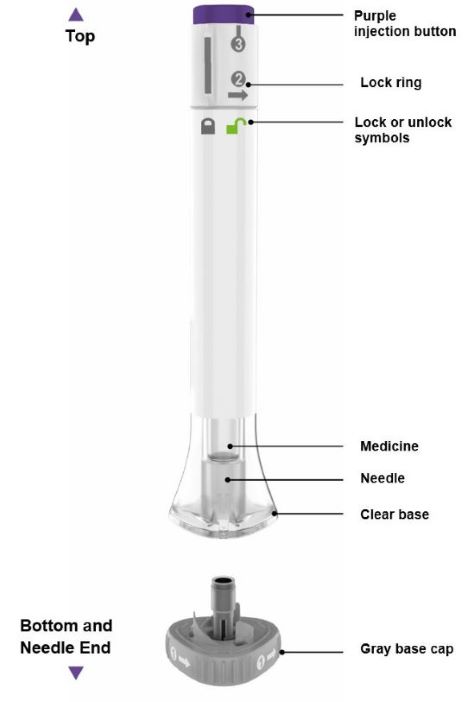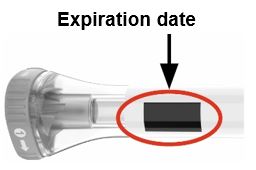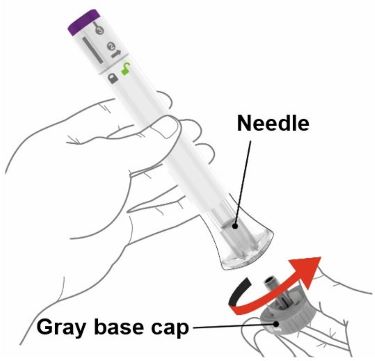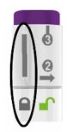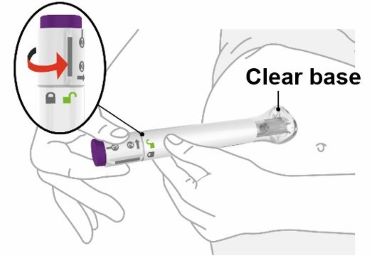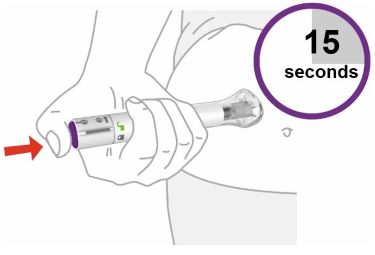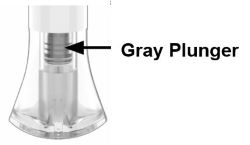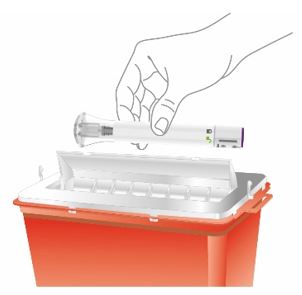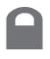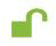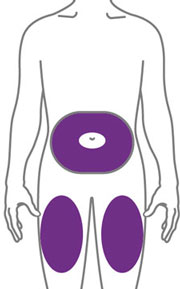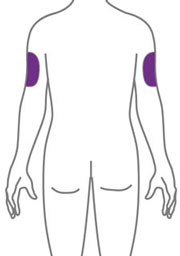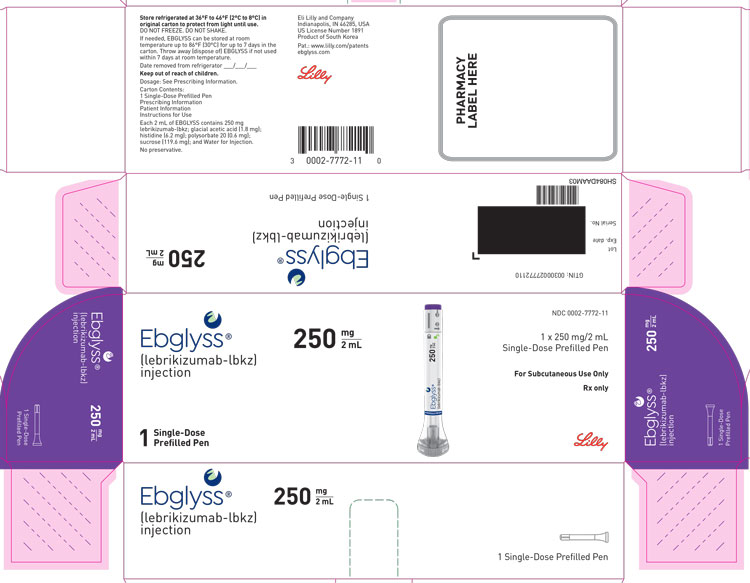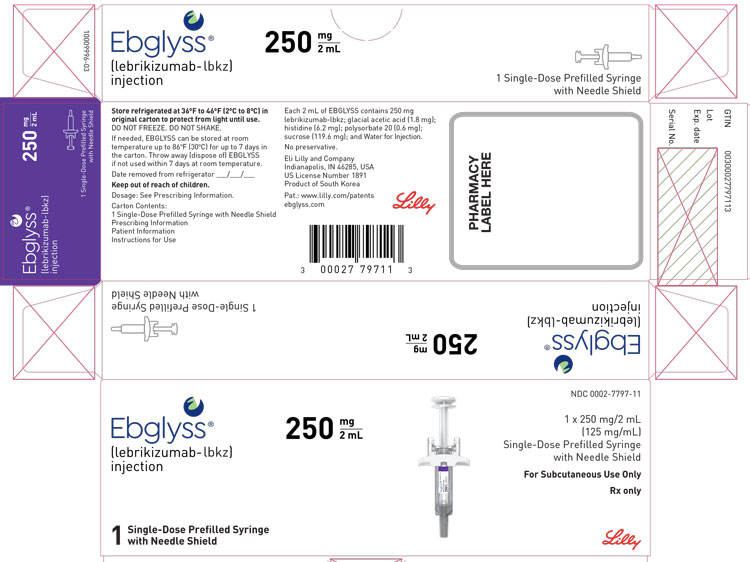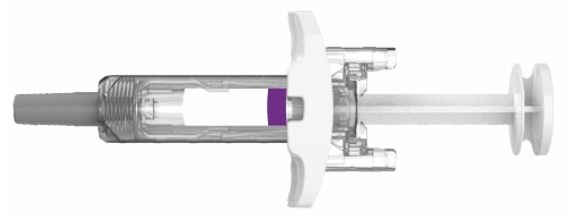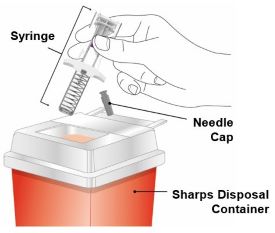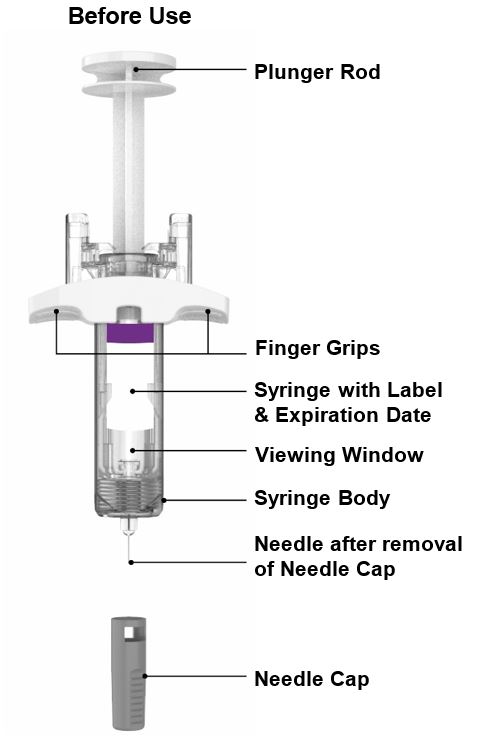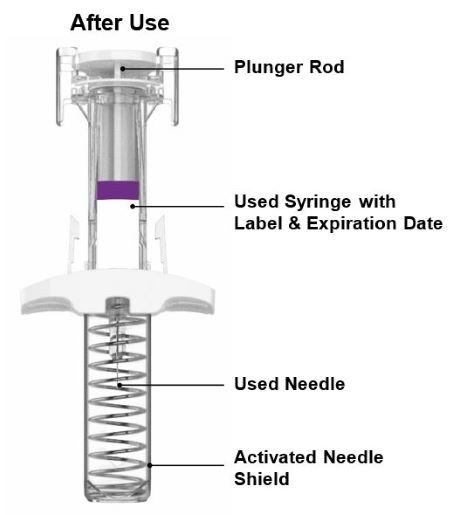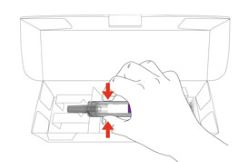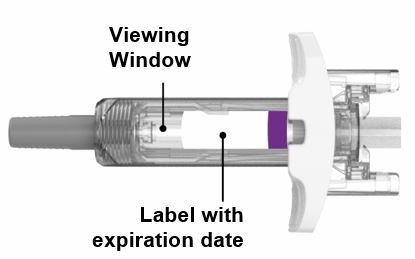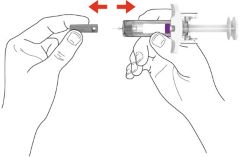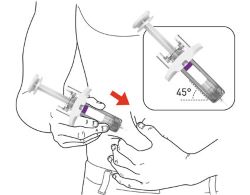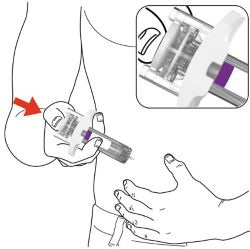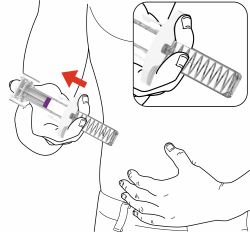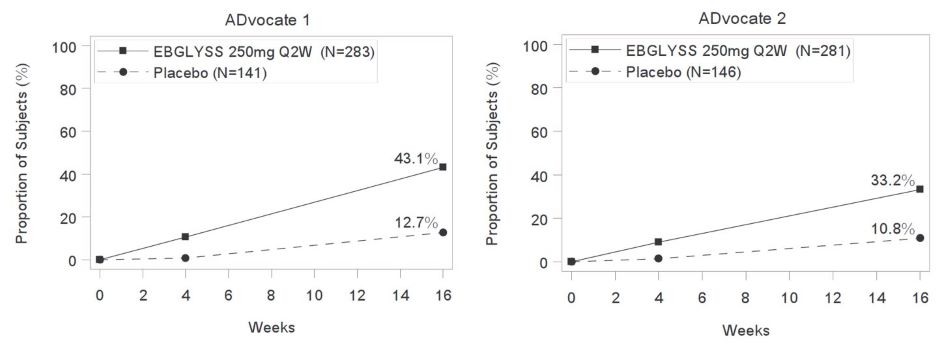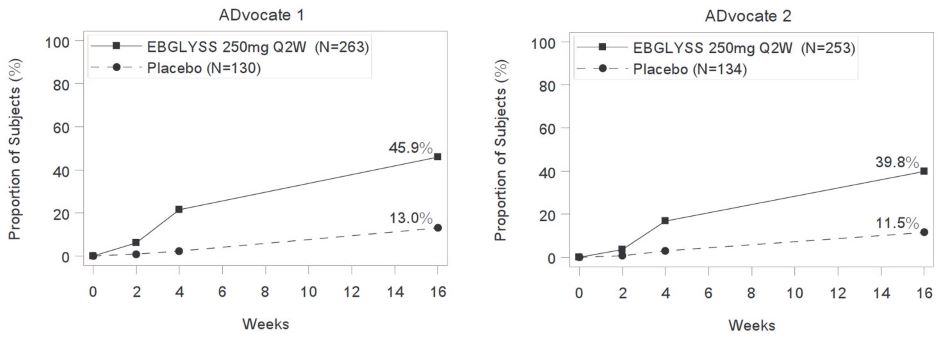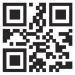 DRUG LABEL: EBGLYSS
NDC: 0002-7772 | Form: INJECTION, SOLUTION
Manufacturer: Eli Lilly and Company
Category: prescription | Type: HUMAN PRESCRIPTION DRUG LABEL
Date: 20251118

ACTIVE INGREDIENTS: Lebrikizumab 250 mg/2 mL
INACTIVE INGREDIENTS: Acetic acid 1.8 mg/2 mL; Histidine 6.2 mg/2 mL; Polysorbate 20 0.6 mg/2 mL; Sucrose 119.6 mg/2 mL; Water

HIGHLIGHTS OF PRESCRIBING INFORMATION

These highlights do not include all the information needed to use EBGLYSS safely and effectively. See full prescribing information for EBGLYSS.
EBGLYSS (lebrikizumab-lbkz), injection, for subcutaneous use
Initial U.S. Approval: 2024

RECENT MAJOR CHANGES

Dosage and Administration, single-dose prefilled pen warming instructions (2.4) removed | 5/2025
Dosage and Administration, single-dose prefilled syringe warming instructions (2.4) removed | 10/2025

1 INDICATIONS AND USAGE

EBGLYSS® is an interleukin-13 antagonist indicated for the treatment of adults and pediatric patients 12 years of age and older who weigh at least 40 kg with moderate-to-severe atopic dermatitis whose disease is not adequately controlled with topical prescription therapies or when those therapies are not advisable. EBGLYSS can be used with or without topical corticosteroids. (1)

2 DOSAGE AND ADMINISTRATION

- Prior to EBGLYSS treatment, complete all age-appropriate vaccinations according to current immunization guidelines. (2.1)
- The recommended dosage of EBGLYSS is 500 mg (two 250 mg injections) at Week 0 and Week 2, followed by 250 mg (one injection) every 2 weeks until Week 16 or later, when adequate clinical response is achieved. The maintenance dose is EBGLYSS 250 mg every 4 weeks. (2.2)
- Administer by subcutaneous injection. (2.4)

3 DOSAGE FORMS AND STRENGTHS

Injection:

- 250 mg/2 mL in a single-dose prefilled pen (3)
- 250 mg/2 mL (125 mg/mL) in a single-dose prefilled syringe with needle shield (3)

4 CONTRAINDICATIONS

Prior serious hypersensitivity to lebrikizumab-lbkz or any excipients in EBGLYSS. (4)

5 WARNINGS AND PRECAUTIONS

- Hypersensitivity: Hypersensitivity reactions including angioedema and urticaria, have occurred after administration of EBGLYSS. Discontinue EBGLYSS in the event of a serious hypersensitivity reaction. (5.1)
- Conjunctivitis and Keratitis: Report new onset or worsening eye symptoms to a healthcare provider. (5.2)
- Parasitic (Helminth) Infections: Treat patients with pre-existing helminth infections before initiating EBGLYSS. If patients become infected while receiving EBGLYSS and do not respond to anti-helminth treatment, discontinue treatment with EBGLYSS until the infection resolves. (5.3)
- Vaccinations: Avoid use of live vaccines during treatment with EBGLYSS. (5.4)

6 ADVERSE REACTIONS

Most common (≥1%) adverse reactions are conjunctivitis, injection site reactions, and herpes zoster. (6.1)

To report SUSPECTED ADVERSE REACTIONS, contact Eli Lilly and Company at 1-800-LillyRx (1-800-545-5979) or FDA at 1-800-FDA-1088 or www.fda.gov/medwatch.

FULL PRESCRIBING INFORMATION

1 INDICATIONS AND USAGE

EBGLYSS is indicated for the treatment of adults and pediatric patients 12 years of age and older who weigh at least 40 kg with moderate-to-severe atopic dermatitis whose disease is not adequately controlled with topical prescription therapies or when those therapies are not advisable. EBGLYSS can be used with or without topical corticosteroids.

2 DOSAGE AND ADMINISTRATION

2.1 Vaccination Prior to Administration of EBGLYSS

Complete all age-appropriate vaccinations according to current immunization guidelines [see Warnings and Precautions (5.4)].

2.2 Recommended Dosage

The recommended dosage of EBGLYSS is an initial dose of 500 mg (two 250 mg injections) at Week 0 and Week 2, followed by 250 mg every two weeks until Week 16 or later, when adequate clinical response is achieved. The maintenance dosage is 250 mg every four weeks [see Clinical Studies (14.1)].

2.3 Concomitant Topical Therapies

EBGLYSS can be used with or without topical corticosteroids (TCS). Topical calcineurin inhibitors (TCI) may be used, but reserved for sensitive areas only, such as the face, neck, intertriginous and genital areas.

2.4 Important Administration Instructions

- EBGLYSS is for subcutaneous administration.
- EBGLYSS is intended for use under the guidance of a healthcare professional. Provide proper training to patients and/or caregivers on the subcutaneous injection technique of EBGLYSS. Adult patients may self-inject, or caregivers may give EBGLYSS after training in subcutaneous injection technique. For pediatric patients, caregivers may give injections after training in subcutaneous injection technique.
- Sites for injection include the abdomen, thigh, and back of the upper arm. Administration of EBGLYSS in the back of the upper arm may be performed by a caregiver or healthcare provider.
- Alternate the injection site with each injection. Do not inject EBGLYSS within 2 inches (5 cm) of the navel or into areas where the skin is tender, bruised, red, hard, or in an area of skin that is affected by atopic dermatitis or skin lesions.
- It is not necessary to allow EBGLYSS prefilled pen or EBGLYSS prefilled syringe to warm up to room temperature before use.
- Parenteral drug products should be inspected visually for particulate matter and discoloration prior to administration, whenever solution and container permit. EBGLYSS is a clear to opalescent, colorless to slightly yellow to slightly brown solution. Do not use if the liquid contains visible particles, is discolored or cloudy [see Dosage Forms and Strengths (3), How Supplied/Storage and Handling (16)].
- Refer to the Instructions for Use for complete administration instructions with illustrations [see Instructions for Use].

2.5 Missed Dose

If a dose is missed, administer the dose as soon as possible. Thereafter, resume dosing at the regular scheduled time.

3 DOSAGE FORMS AND STRENGTHS

EBGLYSS is a clear to opalescent, colorless to slightly yellow to slightly brown solution available as follows:

- Injection: 250 mg/2 mL in a single-dose prefilled pen
- Injection: 250 mg/2 mL (125 mg/mL) in a single-dose prefilled syringe with needle shield

4 CONTRAINDICATIONS

EBGLYSS is contraindicated in patients with prior serious hypersensitivity to lebrikizumab-lbkz or any excipients of EBGLYSS [see Warnings and Precautions (5.1)].

5 WARNINGS AND PRECAUTIONS

5.1 Hypersensitivity

Hypersensitivity reactions, including angioedema and urticaria, have been reported with use of EBGLYSS. If a serious hypersensitivity reaction occurs, discontinue EBGLYSS and institute appropriate therapy.

5.2 Conjunctivitis and Keratitis

Conjunctivitis and keratitis adverse reactions have been reported in clinical trials.

Conjunctivitis and keratitis occurred more frequently in atopic dermatitis subjects who received EBGLYSS compared to those who received placebo. Conjunctivitis was the most frequently reported eye disorder. Most subjects with conjunctivitis or keratitis recovered during the treatment period [see Adverse Reactions (6.1)].

Advise patients to report new onset or worsening eye symptoms to their healthcare provider.

5.3 Parasitic (Helminth) Infections

Patients with known helminth infections were excluded from participation in clinical studies. It is unknown if EBGLYSS will influence the immune response against helminth infections by inhibiting IL-13 signaling.

Treat patients with pre-existing helminth infections before initiating treatment with EBGLYSS. If patients become infected while receiving EBGLYSS and do not respond to antihelminth treatment, discontinue treatment with EBGLYSS until the infection resolves.

5.4 Vaccinations

EBGLYSS may alter a patient’s immunity and increase the risk of infection following administration of live vaccines. Prior to therapy with EBGLYSS, complete all age-appropriate vaccinations according to current immunization guidelines. Avoid use of live vaccines immediately prior to or during treatment with EBGLYSS. No data are available on the response to live vaccines.

6 ADVERSE REACTIONS

The following adverse reactions are described elsewhere in the labeling:

- Hypersensitivity [see Warnings and Precautions (5.1)]
- Conjunctivitis and Keratitis [see Warnings and Precautions (5.2)]

6.1 Clinical Trials Experience

Because clinical trials are conducted under widely varying and controlled conditions, adverse reaction rates observed in the clinical trials of a drug cannot be directly compared to rates in the clinical trials of another drug and may not reflect the rates observed in practice.

Atopic Dermatitis

The safety of EBGLYSS was evaluated across 4 randomized, double-blind, placebo-controlled, multicenter trials in subjects with moderate-to-severe atopic dermatitis including 3 phase 3 trials (ADvocate 1, ADvocate 2, ADhere) and 1 phase 2 dose ranging trial (KGAF). In these 4 trials, mean age was 37 years; 50% of subjects were male; 62% were White, 13% were Black, and 20% were Asian. In terms of co-morbid conditions, in the phase 3 trials, 30% of the subjects had asthma, 50% had allergic rhinitis, 31% had food allergy, and 14% had allergic conjunctivitis at baseline.

A total of 891 subjects were treated with EBGLYSS for at least 1 year in the atopic dermatitis development program.

ADvocate 1, ADvocate 2, and KGAF compared the safety of EBGLYSS monotherapy to placebo. ADhere compared the safety of EBGLYSS + TCS to placebo + TCS through 16 weeks. All subjects from the phase 3 trials were allowed to enroll in the long-term extension study.

Weeks 0 to 16

Table 1 summarizes the adverse reactions that occurred at a rate of at least 1% in the EBGLYSS 250 mg every 2 weeks monotherapy group, or in the EBGLYSS 250 mg every 2 weeks + TCS group, all at a higher rate than placebo during the first 16 weeks of treatment.

Table 1: Adverse Reactions Occurring in ≥1% of the EBGLYSS Monotherapy Group or the EBGLYSS + TCS Group in the Atopic Dermatitis Trials through Week 16
Adverse Reactions | EBGLYSS Monotherapya |  | EBGLYSS + TCSb
Adverse Reactions | EBGLYSS 250 mg Q2Wc N = 638 n (%) | Placebo N = 338 n (%) | EBGLYSS 250 mg Q2Wc + TCS N = 145 n (%) | Placebo + TCS N = 66 n (%)
Conjunctivitisd | 61 (10) | 10 (3) | 7 (5) | 0
Injection Site Reactionse | 16 (3) | 4 (1) | 4 (3) | 1 (2)
Herpes Zoster | 3 (<1) | 0 | 2 (1) | 0
a Integrated analysis of ADvocate 1, ADvocate 2, and the phase 2 dose finding trial (KGAF)
b Analysis of TCS concomitant therapy trial ADhere
c EBGLYSS 500 mg at Week 0 and Week 2, followed by 250 mg every two weeks
d Conjunctivitis cluster includes conjunctivitis, conjunctivitis allergic, and conjunctivitis bacterial
e Injection Site Reactions cluster includes injection site-related: pain, erythema, reaction, discomfort, dermatitis, pruritus, swelling, and rash

In the monotherapy trials (ADvocate 1, ADvocate 2, and KGAF) through Week 16, the proportion of subjects who discontinued treatment due to adverse events was 2.4% in the EBGLYSS 250 mg every 2 weeks group and 1.8% in the placebo group. In the TCS trial (ADhere) through Week 16, the proportion of subjects who discontinued treatment due to adverse events was 2.1% in the EBGLYSS 250 mg every 2 weeks + TCS group and 0% in the placebo + TCS group. The most common adverse reactions leading to discontinuation of EBGLYSS compared to the placebo group were conjunctivitis and keratitis (0.6% vs. 0.3%), and injection site reactions (0.2% vs. 0) in the monotherapy trials; and conjunctivitis (0.7% vs. 0), and injection site reactions (0.7% vs. 0) in the TCS trial.

Eosinophilia

Increased post-baseline blood eosinophils were observed at a higher frequency in EBGLYSS-treated subjects compared to placebo. During the first 16 weeks, eosinophilia (>5000 cells/mcL) was observed in 0.4% in the EBGLYSS-treated subjects and 0% in subjects receiving placebo. Blood eosinophil elevations were generally transient and did not result in discontinuation.

Safety Weeks 16 to 52

Among those EBGLYSS-treated subjects who responded at Week 16 and who were re-randomized in the maintenance period of the monotherapy trials ADvocate 1 and ADvocate 2, a total of 113 and 118 subjects received EBGLYSS 250 mg every 2 weeks or every 4 weeks, respectively. The safety profile of EBGLYSS 250 mg every 4 weeks was generally consistent with EBGLYSS every 2 weeks during Weeks 16 to 52. The safety profile of EBGLYSS during maintenance treatment was generally consistent with the safety profile observed through Week 16.

Specific Adverse Drug Reactions

Conjunctivitis and Keratitis

Conjunctivitis was the most frequently reported eye disorder. Most cases of conjunctivitis and keratitis were mild or moderate in severity and recovered or resolved without treatment interruption or discontinuation.

During the initial 16-week treatment period of the monotherapy trials, conjunctivitis, including allergic conjunctivitis, was reported by 61 subjects (10%) in the EBGLYSS 250 mg every 2 weeks group and 10 subjects (3%) in the placebo group. In the TCS concomitant therapy trial, conjunctivitis was reported by 7 subjects (5%) in the EBGLYSS 250 mg every 2 weeks + TCS group compared to 0% in the placebo + TCS group. During the 16-week placebo-controlled induction period, 68 subjects reported 73 events of conjunctivitis. All events were nonserious and mild or moderate in severity. Conjunctivitis led to treatment discontinuation in 3 subjects. The exposure adjusted incidence rate of conjunctivitis for subjects treated with EBGLYSS 250 mg every 2 weeks was 30.6 events per 100 patient years through Week 16 (KGAF, ADvocate 1, ADvocate 2, ADhere).

During the maintenance treatment period of the monotherapy trials (ADvocate 1 and ADvocate 2) from 16 to 52 weeks, conjunctivitis, including allergic conjunctivitis, was reported by 2 subjects (1.8%) in the EBGLYSS 250 mg every 2 weeks group and 12 subjects (10.1%) in the EBGLYSS 250 mg every 4 weeks group, compared to 5 subjects (8.3%) in the placebo group. During the maintenance treatment period, 14 subjects treated with EBGLYSS reported 18 events of conjunctivitis. All events were mild or moderate in severity. Conjunctivitis led to treatment discontinuation in 2 subjects in the EBGLYSS 250 mg every 4 weeks group. The exposure adjusted incidence rate of conjunctivitis for subjects treated with EBGLYSS 250 mg every 2 weeks was 18.3 events per 100 patient years and for those treated with EBGLYSS 250 mg every 4 weeks was 20.6 events per 100 patient years through Week 52 (ADvocate 1, ADvocate 2, ADhere + the long-term extension study).

During the initial 16-week treatment period of the monotherapy trials, keratitis, including atopic and vernal keratoconjunctivitis, was reported by 4 subjects (0.6%) in the EBGLYSS 250 mg every 2 weeks group and 1 subject (0.3%) in the placebo group. In the TCS concomitant therapy trial, vernal keratoconjunctivitis was reported by 1 subject (0.7%) in the EBGLYSS 250 mg every 2 weeks + TCS group, compared to 0% in the placebo + TCS group. All events were nonserious and mild or moderate in severity. Keratitis led to treatment discontinuation in 2 subjects. The exposure adjusted incidence rate of keratitis for subjects treated with EBGLYSS 250 mg every 2 weeks was 2.2 events per 100 patient years through Week 16 (KGAF, ADvocate 1, ADvocate 2, ADhere).

During the maintenance treatment period of the monotherapy trials (ADvocate 1 and ADvocate 2) from 16 to 52 weeks, atopic keratoconjunctivitis was reported by 1 subject (0.8%) in the EBGLYSS 250 mg every 4 weeks group, and vernal keratoconjunctivitis was reported by 1 subject (0.9%) in the EBGLYSS 250 mg every 2 weeks group, compared to 0% in the placebo group. One (0.9%) event of severe vernal keratoconjunctivitis in an EBGLYSS 250 mg every 2 weeks subject led to treatment discontinuation. The exposure adjusted incidence rate of keratitis for subjects treated with EBGLYSS 250 mg every 2 weeks was 1.0 event per 100 patient years and for those treated with EBGLYSS 250 mg every 4 weeks was 0.7 events per 100 patient years through Week 52 (ADvocate 1, ADvocate 2, ADhere + the long-term extension study).

Injection Site Reactions

Injection site reactions were reported by 3% of the EBGLYSS group and 1% of the placebo group in the first 16 weeks of the monotherapy trials. Incidence of injection site reactions declined with continued treatment. Most events were mild or moderate and recovered without treatment discontinuation.

8 USE IN SPECIFIC POPULATIONS

8.1 Pregnancy

Risk Summary

Available data on lebrikizumab-lbkz use in pregnant women are insufficient to evaluate for a drug-associated risk of major birth defects, miscarriage, or other adverse maternal or fetal outcomes. Monoclonal antibodies are actively transported across the placenta (see Clinical Considerations). In animal reproduction studies, no effects on embryo-fetal development were observed after subcutaneous administration of lebrikizumab-lbkz to cynomolgus monkeys during organogenesis at doses up to 18 times the human exposure at the maximum recommended human dose (MRHD) (see Data).

All pregnancies have a background risk of birth defect, loss, or other adverse outcomes. The background risk of major birth defects and miscarriage for the indicated population is unknown. In the U.S. general population, the estimated background risk of major birth defects and miscarriage in clinically recognized pregnancies is 2 to 4% and 15 to 20%, respectively.

Report pregnancies to Eli Lilly and Company at 1-800-LillyRx (1-800-545-5979).

Clinical Considerations

Fetal/Neonatal Adverse Reactions

Transport of endogenous IgG antibodies across the placenta increases as pregnancy progresses and peaks during the third trimester. Therefore, EBGLYSS may be present in infants exposed in utero. The potential clinical impact of EBGLYSS exposure in infants exposed in utero should be considered.

Data

Animal Data

In an embryofetal development study, no malformations or embryofetal toxicity were observed in fetuses from pregnant cynomolgus monkeys administered lebrikizumab-lbkz during organogenesis at doses up to 150 mg/kg initial dose followed by 50 mg/kg per week by subcutaneous injection, which was associated with plasma exposure (Cavg,ss) approximately 18 times the human exposure at the MRHD. Lebrikizumab-lbkz crossed the placenta in monkeys.

In a prenatal and postnatal development study, pregnant cynomolgus monkeys were administered lebrikizumab-lbkz during organogenesis to parturition at doses up to 150 mg/kg initial dose followed by 50 mg/kg per week by subcutaneous injection, which was associated with plasma exposure (Cavg,ss) approximately 18 times the human exposure at the MRHD. No embryofetal toxicity or malformations, or effects on morphological, functional, or immunological development were observed in the infants from birth through 6 months of age.

8.2 Lactation

Risk Summary

There are no data on the presence of lebrikizumab-lbkz in human milk, the effects on the breastfed infant, or the effects on milk production. Endogenous IgG and monoclonal antibodies are transferred in human milk. The effects of local gastrointestinal exposure and limited systemic exposure in the breastfed infant to lebrikizumab-lbkz are unknown. The developmental and health benefits of breastfeeding should be considered along with the mother's clinical need for EBGLYSS and any potential adverse effects on the breastfed infant from EBGLYSS or from the underlying maternal condition.

8.4 Pediatric Use

The safety and effectiveness of EBGLYSS have been established in pediatric patients 12 years of age and older who weigh at least 40 kg with moderate-to-severe atopic dermatitis whose disease is not adequately controlled with topical prescription therapies or when those therapies are not advisable. A total of 372 pediatric subjects were exposed to EBGLYSS with 270 subjects exposed to EBGLYSS for at least one year. The safety and effectiveness were generally consistent between pediatric and adult subjects [see Adverse Reactions (6.1), Clinical Studies (14.1)].

The safety and effectiveness of EBGLYSS have not been established in pediatric patients younger than 12 years of age and pediatric patients 12 years and older who weigh less than 40 kg.

8.5 Geriatric Use

Of the 1348 adult subjects with moderate-to-severe atopic dermatitis exposed to EBGLYSS, a total of 123 were 65 years or older, and 29 subjects were 75 years or older. Clinical studies of EBGLYSS did not include sufficient numbers of subjects 65 years of age and older to determine whether they respond differently from younger adult subjects [see Clinical Pharmacology (12.3)].

10 OVERDOSAGE

In the event of overdosage, contact Poison Control (1-800-222-1222) for the latest recommendations and monitor the patient for any signs or symptoms of adverse reactions and institute appropriate symptomatic treatment immediately.

11 DESCRIPTION

Lebrikizumab-lbkz, an interleukin-13 antagonist, is an immunoglobulin G4 (IgG4) monoclonal antibody that binds to interleukin (IL)-13 and inhibits IL-13 signaling. Lebrikizumab-lbkz is produced in Chinese Hamster Ovary (CHO) cells by recombinant DNA technology. Lebrikizumab-lbkz has an approximate molecular weight of 145 kDa.

EBGLYSS (lebrikizumab-lbkz) injection is a sterile, preservative free, clear to opalescent, colorless to slightly yellow to slightly brown solution for subcutaneous use. EBGLYSS is available as either a 250 mg/2 mL single-dose prefilled pen or a single-dose prefilled syringe with needle shield. The EBGLYSS prefilled pen and prefilled syringe with needle shield are not made with natural rubber latex.

Each prefilled pen or prefilled syringe delivers 250 mg lebrikizumab-lbkz in 2 mL solution which also contains glacial acetic acid (1.8 mg), histidine (6.2 mg), polysorbate 20 (0.6 mg), sucrose (119.6 mg) and Water for Injection. The pH is 5.4 – 6.0.

12 CLINICAL PHARMACOLOGY

12.1 Mechanism of Action

Lebrikizumab-lbkz is an IgG4 monoclonal antibody that binds with high affinity and slow off-rate to interleukin (IL)-13 and allows IL-13 to bind to IL-13Rα1 but inhibits human IL-13 signaling through the IL-4Rα/IL-13Rα1 receptor complex. IL-13 is a naturally occurring cytokine that is involved in Type 2 inflammation, which is an important component in the pathogenesis of atopic dermatitis. Lebrikizumab-lbkz inhibits IL-13-induced responses including the release of proinflammatory cytokines, chemokines and IgE. Lebrikizumab-lbkz-bound IL-13 can still bind IL-13Rα2 allowing subsequent internalization and natural clearance of IL-13.

12.2 Pharmacodynamics

In clinical studies, lebrikizumab-lbkz reduced the levels of serum periostin, total immunoglobulin E (IgE), CC chemokine ligand (CCL)17 [thymus and activation-regulated chemokine (TARC)], CCL18 [pulmonary and activation-regulated chemokine (PARC)], and CCL13 [monocyte chemotactic protein-4 (MCP-4)]. The clinical relevance of these biomarkers is not completely understood.

12.3 Pharmacokinetics

Lebrikizumab-lbkz steady-state exposure following either a subcutaneous dose of 250 mg every 2 weeks or every 4 weeks in patients with atopic dermatitis are presented in Table 2. Lebrikizumab-lbkz exposure increases dose-proportionally over a subcutaneous dose range of 37.5 to 500 mg. Lebrikizumab-lbkz steady state is achieved at Week 4 following the approved recommended loading doses.

Table 2: Lebrikizumab-lbkz Steady-State Exposure Following Subcutaneous Administration in Patients with Atopic Dermatitis
Lebrikizumab-lbkz Dosagea | Cmax | Cavg | Ctrough
250 mg every 2 weeks | 108 mcg/mL | 100 mcg/mL | 87 mcg/mL
250 mg every 4 weeks | 63 mcg/mL | 51 mcg/mL | 36 mcg/mL
Cmax = Maximum concentration, Cavg = Average concentration, Ctrough = Trough concentration
a Following approved recommended loading doses

Absorption

Following a single subcutaneous 250 mg dose of lebrikizumab-lbkz, peak serum concentrations were achieved approximately 7 to 8 days post dose. The absolute bioavailability for a subcutaneous dose was approximately 86%.

Injection site locations did not influence the absorption of lebrikizumab-lbkz.

Distribution

The lebrikizumab-lbkz steady-state volume of distribution is 5.14 L.

Metabolism/Elimination

Lebrikizumab-lbkz is expected to be degraded into small peptides and amino acids via catabolic pathways in the same manner as endogenous IgG.

The lebrikizumab-lbkz half-life is 24.5 days and clearance is 0.154 L/day. Lebrikizumab-lbkz exhibits linear elimination that is independent of dose.

Specific Populations

Age, Sex, Race

Age, sex, or race did not have a significant effect on the pharmacokinetics of lebrikizumab-lbkz.

Weight

Lebrikizumab-lbkz trough concentrations were lower in subjects with higher body weight.

Patients with Renal or Hepatic Impairment

Specific clinical pharmacology studies to evaluate the effects of renal impairment and hepatic impairment on the pharmacokinetics of lebrikizumab-lbkz have not been conducted. Lebrikizumab-lbkz, as a monoclonal antibody, is not expected to undergo significant hepatic or renal elimination. No clinically significant differences in the pharmacokinetics of lebrikizumab-lbkz were observed in patients with mild or moderate renal impairment.

Drug Interaction Studies

The effect of lebrikizumab-lbkz on the PK of co-administered medications has not been studied.

12.6 Immunogenicity

The observed incidence of anti-drug antibodies is highly dependent on the sensitivity and specificity of the assay. Differences in assay methods preclude meaningful comparisons of the incidence of anti-drug antibodies in the studies described below with the incidence of anti-drug antibodies in other studies, including those of EBGLYSS or of other drug products.

Antibodies to lebrikizumab-lbkz developed in 4/145 (2.8%) of subjects treated with EBGLYSS 250 mg every 2 weeks followed by 250 mg every four weeks during the 12-month treatment period in EBGLYSS studies. Most of these antibodies were neutralizing and of low titer. Similar results were observed in pediatric subjects who received EBGLYSS up to 12 months. The presence of anti-drug antibodies was not associated with changes to pharmacokinetics, efficacy, or safety of lebrikizumab-lbkz. The clinical relevance of these findings is unknown because of the low occurrence of ADA.

13 NONCLINICAL TOXICOLOGY

13.1 Carcinogenesis, Mutagenesis, Impairment of Fertility

Animal studies have not been conducted to evaluate the carcinogenic or mutagenic potential of lebrikizumab-lbkz.

No effects on fertility parameters such as reproductive organs, reproductive hormones or menstrual cycle length were observed in sexually mature female cynomolgus monkeys that were administered intravenous doses of lebrikizumab-lbkz up to 25 mg/kg/week for 37 weeks, which was associated with plasma exposure (Cavg,ss) approximately 15 times the human exposure at the MRHD. No effects on reproductive organs or sperm analysis were observed in sexually mature male cynomolgus monkeys that were administered subcutaneous doses of lebrikizumab-lbkz up to 25 mg/kg/week for 13 weeks, which was associated with plasma exposure (Cavg,ss) approximately 11 times the human exposure at the MRHD.

14 CLINICAL STUDIES

14.1 Atopic Dermatitis

Three multicenter, randomized, double-blind, placebo-controlled trials, ADvocate 1, ADvocate 2 and ADhere (NCT04146363, NCT04178967, NCT04250337) enrolled a total of 1062 subjects 12 years of age and older with moderate-to-severe atopic dermatitis not adequately controlled by topical medication(s) and who were candidates for systemic therapy. A total of 148 subjects (14%) were 12 to <18 years who weighed at least 40 kg and 914 (86%) were adult subjects. Disease severity was defined by an Investigator's Global Assessment (IGA) score ≥3 in the overall assessment of AD lesions on a severity scale of 0 to 4, an Eczema Area and Severity Index (EASI) score ≥16 on a scale of 0 to 72, and a minimum body surface area involvement of ≥10%.

At baseline, 50% of subjects were male, 63% were White, 11% were Black or African American, and 21% were Asian; 12.8% identified as Hispanic or Latino, 63% of subjects had a baseline IGA score of 3 (moderate AD) and 37% of subjects had a baseline IGA of 4 (severe AD). The baseline mean EASI was 29, and the baseline Pruritus Numeric Rating Scale (NRS) was 7 on a scale of 0-10. Of all subjects, 99% had received prior treatment for AD.

In all three trials, subjects in the EBGLYSS group received subcutaneous injections of EBGLYSS 500 mg at Week 0 and at Week 2, followed by 250 mg every other week (Q2W) through Week 16.

To evaluate the maintenance and durability of response in the monotherapy trials (ADvocate 1 and ADvocate 2), subjects originally randomized to EBGLYSS who achieved an IGA score of 0 or 1, or at least a 75% reduction in EASI from baseline [EASI-75] at Week 16 and did not require rescue therapy were re-randomized to an additional 36 weeks of either a maintenance dose of EBGLYSS 250 mg Q2W (every 2 weeks), EBGLYSS 250 mg Q4W (every 4 weeks), or placebo.

Subjects who did not achieve IGA 0 or 1 or EASI-75 at Week 16 or subjects who required rescue therapy during the first 16 weeks were treated with open-label EBGLYSS 250 mg Q2W.

In the concomitant therapy trial (ADhere), subjects received EBGLYSS + TCS or placebo + TCS. Topical calcineurin inhibitors (TCI) were permitted for sensitive areas only, such as the face, neck, intertriginous and genital areas.

All three trials assessed the primary endpoint, the proportion of subjects who achieved an IGA score of 0 (clear) or 1 (almost clear) and at least a 2-point improvement from baseline at Week 16. Other evaluated outcomes at Week 16 included the proportion of subjects with EASI-75 and EASI-90, and improvement in itch severity as defined by a reduction of at least 4 points on an 11-point Pruritus NRS. ADvocate 1 and ADvocate 2 also evaluated the maintenance and durability of response through Week 52.

The results of the EBGLYSS monotherapy trials (ADvocate 1 and ADvocate 2) are presented in Table 3.

Table 3: Efficacy Results of EBGLYSS Monotherapy at Week 16a in ADvocate 1 and ADvocate 2 in Subjects with Moderate-to-Severe Atopic Dermatitis
 | ADvocate 1 |  |  | ADvocate 2
 | EBGLYSS 250 mg Q2Wb | Placebo | Difference from Placebo (95% CI) | EBGLYSS 250 mg Q2Wb | Placebo | Difference from Placebo (95% CI)
Number of subjects | 283 | 141 | -- | 281 | 146 | --
IGA 0 or 1c | 43% | 13% | 30% (22%, 38%) | 33% | 11% | 22% (14%, 30%)
EASI-75 | 59% | 16% | 42% (33%, 51%) | 52% | 18% | 33% (24%, 42%)
EASI-90 | 38% | 9% | 29% (21%, 36%) | 31% | 10% | 21% (13%, 28%)
Number of subjects with baseline Pruritus NRS score ≥4 | 263 | 130 | -- | 253 | 134 | --
Pruritus NRS ≥4 point improvement | 46% | 13% | 33% (25%, 41%) | 40% | 12% | 28% (20%, 37%)
a Subjects who received rescue therapy or discontinued treatment due to lack of efficacy were analyzed as non-responders. Data after treatment discontinuation due to any other reason were considered missing. Any missing data was imputed using MCMC-MI.
b Subjects received 500 mg of EBGLYSS at Week 0 and Week 2, and 250 mg Q2W up to Week 16
c Primary endpoint. Responder was defined as a subject with an IGA 0 or 1 (“clear” or “almost clear”) and a reduction of ≥2 points on a 0-4 IGA scale

The proportion of EBGLYSS-treated subjects who achieved IGA 0 or 1 (with ≥2-point improvement from baseline) by visit in ADvocate 1 and ADvocate 2 are presented in Figure 1.

Figure 1: Proportion of Subjects with Moderate-to-Severe Atopic Dermatitis achieving IGA 0 or 1, with a ≥2-point improvement from baseline through Week 16 in ADvocate 1 and ADvocate 2

The proportion of EBGLYSS-treated subjects who achieved at least a 4-point improvement from baseline in Pruritus NRS by visit in ADvocate 1 and ADvocate 2 are presented in Figure 2.

Figure 2: Proportion of Subjects with Moderate-to-Severe Atopic Dermatitis with ≥4-point improvement in Pruritus NRS through Week 16 in ADvocate 1 or ADvocate 2

Examination of age, sex, and White, Asian, Black or African American race subgroups did not identify differences in response to EBGLYSS among these subgroups. The database was not large enough to adequately assess differences in effects in other races.

The results in the concomitant therapy trial (ADhere) at Week 16, where subjects received EBGLYSS + TCS or placebo + TCS were consistent with the results in the monotherapy trials (ADvocate 1 and ADvocate 2).

Maintenance and Durability of Response (Week 16 to Week 52)

EBGLYSS-treated subjects achieving IGA 0 or 1 or EASI-75, and who did not receive rescue therapy at Week 16 were re-randomized to 36 weeks of maintenance treatment with EBGLYSS 250 mg Q2W, EBGLYSS 250 mg Q4W, or placebo in ADvocate 1 and ADvocate 2. The results are presented in Table 4.

Table 4: Efficacy Results of EBGLYSS at Week 52 in ADvocate 1 and ADvocate 2a in Subjects with Moderate-to-Severe Atopic Dermatitis
 | ADvocate 1 |  |  | ADvocate 2
 | EBGLYSS 250 mg Q2W | EBGLYSS 250 mg Q4W | Placebo | EBGLYSS 250 mg Q2W | EBGLYSS 250 mg Q4W | Placebo
Number of subjects who were IGA of 0 or 1 Responders at Week 16 b | 45 | 45 | 22 | 32 | 32 | 16
IGA of 0 or 1b at Week 52 | 76% | 74% | 47% | 65% | 81% | 50%
Number of subjects who were EASI-75 Responders at Week 16 | 61 | 62 | 30 | 51 | 53 | 27
EASI-75 at Week 52 | 79% | 79% | 61% | 77% | 85% | 72%
a Subjects who received systemic rescue therapy, discontinued treatment due to lack of efficacy were analyzed as non-responders. Data after topical rescue medication or treatment discontinuation due to any other reason were considered missing. Any missing data were imputed using MCMC-MI.
b Responder was defined as a subject with an IGA 0 or 1 (“clear” or “almost clear”) and a reduction of ≥2 points on a 0-4 IGA scale

16 HOW SUPPLIED/STORAGE AND HANDLING

How Supplied

EBGLYSS (lebrikizumab-lbkz) injection is a sterile, preservative free, clear to opalescent, colorless to slightly yellow to slightly brown solution, available in a single-dose prefilled pen or a single-dose prefilled syringe with needle shield. Each prefilled pen and prefilled syringe with needle shield is designed to deliver 250 mg of EBGLYSS in 2 mL.

EBGLYSS is supplied as:

 | Pack Size | NDC
Prefilled Pen
250 mg/2 mL single-dose | Carton of 1 | 0002-7772-11
Prefilled syringe with needle shield
250 mg/2 mL (125 mg/mL) single-dose | Carton of 1 | 0002-7797-11

Storage and Handling

Store refrigerated at 2°C to 8°C (36°F to 46°F).

If necessary, EBGLYSS can be stored at room temperature up to 30°C (86°F) for up to 7 days in the original carton. Dispose of EBGLYSS that has been left at room temperature for longer than 7 days.

Store in the original carton to protect from light until use.

Do not freeze. Do not use EBGLYSS if it has been frozen.

Do not shake.

Do not microwave, run hot water over it, or leave it in direct sunlight.

Not made with natural rubber latex.

Discard the EBGLYSS single-dose prefilled pen or prefilled syringe with needle shield after use in a puncture-resistant container.

17 PATIENT COUNSELING INFORMATION

Advise the patient and/or caregiver to read the FDA-approved patient labeling (Patient Information and Instructions for Use).

Administration Instructions: Provide guidance to patients and caregivers on proper subcutaneous injection technique, including aseptic technique, and how to use the prefilled pen and prefilled syringe correctly. Advise patients to follow sharps disposal recommendations [see Dosage and Administration (2.4), Instructions for Use].

Hypersensitivity: Advise patients to discontinue EBGLYSS and to seek immediate medical attention if they experience any symptoms of systemic hypersensitivity reactions [see Warnings and Precautions (5.1)].

Conjunctivitis and Keratitis: Advise patients to consult their healthcare provider if new onset or worsening eye symptoms develop [see Warnings and Precautions (5.2)].

Parasitic (Helminth) Infections: Advise patients to notify their healthcare provider if they present with clinical features consistent with helminthic infection [see Warnings and Precautions (5.3)].

Vaccinations: Advise patients that EBGLYSS may increase the risk of infection following administration of live vaccines and that vaccination with live vaccines is not recommended during EBGLYSS treatment. Instruct patients to inform the healthcare provider that they are taking EBGLYSS prior to a potential vaccination [see Warnings and Precautions (5.4)].

Pregnancy: Inform patients to report their pregnancy to Eli Lilly and Company at 1-800-LillyRx (1-800-545-5979) [see Use in Specific Populations (8.1)].

Eli Lilly and Company, Indianapolis, IN 46285, USA

US License No. 1891

Copyright © 2024, 2025, Eli Lilly and Company. All rights reserved.

EBG-0005-USPI-20251028

PATIENT INFORMATION
EBGLYSSTM (EHB-glihs)
(lebrikizumab-lbkz)
injection, for subcutaneous use

What is EBGLYSS?
EBGLYSS is a prescription medicine used to treat adults and children 12 years of age and older who weigh at least 88 pounds (40 kg) with moderate-to-severe eczema (atopic dermatitis) that is not well controlled with prescription therapies used on the skin (topical), or who cannot use topical therapies. EBGLYSS can be used with or without topical corticosteroids.
It is not known if EBGLYSS is safe and effective in children less than 12 years of age or in children 12 years to less than 18 years of age who weigh less than 88 pounds (40 kg).

Do not use EBGLYSS if you are allergic to lebrikizumab-lbkz or to any of the ingredients in EBGLYSS. See the end of this leaflet for a complete list of ingredients in EBGLYSS.

Before you use EBGLYSS, tell your healthcare provider about all your medical conditions, including if you:

- have a parasitic (helminth) infection
- are scheduled to receive any vaccinations. You should not receive a “live vaccine” if you are treated with EBGLYSS.
- are pregnant or plan to become pregnant. It is not known if EBGLYSS will harm your unborn baby. If you become pregnant during treatment with EBGLYSS, you or your healthcare provider can call Eli Lilly and Company at 1-800-LillyRx (1-800-545-5979) to report the pregnancy.
- are breastfeeding or plan to breastfeed. It is not known if EBGLYSS passes into your breast milk.

Tell your healthcare provider about all the medicines you take, including prescription and over-the-counter medicines, vitamins, and herbal supplements.

How should I take EBGLYSS?

- See the detailed “Instructions for Use” that comes with EBGLYSS for information about how to prepare and inject EBGLYSS and how to properly store and throw away (dispose of) used EBGLYSS prefilled pens and prefilled syringes.
- Use EBGLYSS exactly as prescribed by your healthcare provider.
- Your healthcare provider will tell you how much EBGLYSS to inject and how often to inject it.
- EBGLYSS comes as a single-dose prefilled pen or prefilled syringe with needle shield.
- EBGLYSS is given as an injection under the skin (subcutaneous injection).
- If your healthcare provider decides that you or a caregiver can give the injections of EBGLYSS, you or a caregiver should receive training on the right way to prepare and inject EBGLYSS. Do not try to inject EBGLYSS until you have been shown the right way by your healthcare provider. In children 12 years of age and older, EBGLYSS should be given by a caregiver.
- If you miss a dose of EBGLYSS, inject the missed dose as soon as possible, then inject your next dose at your regular scheduled time.
- If you inject too much EBGLYSS (overdose), get medical help or contact a Poison Center expert right away at 1‑800-222-1222.
- Your healthcare provider may prescribe other medicines to use with EBGLYSS. Use the other prescribed medicines exactly as your healthcare provider tells you to.

What are the possible side effects of EBGLYSS?
EBGLYSS can cause serious side effects, including:

- Allergic reactions. EBGLYSS can cause allergic reactions that may sometimes be severe. Stop using EBGLYSS and tell your healthcare provider or get emergency help right away if you get any of the following signs or symptoms:

- breathing problems or wheezing
- swelling of the face, lips, mouth, tongue, or throat

- hives
- itching
- fainting, dizziness, feeling lightheaded

- skin rash
- cramps in your stomach area (abdomen)

- Eye problems. Tell your healthcare provider if you have any new or worsening eye problems, include eye pain or changes in vision, such as blurred vision.

The most common side effects of EBGLYSS include:

- eye and eyelid inflammation, including redness, swelling, and itching

- injection site reactions
- shingles (herpes zoster)

These are not all of the possible side effects of EBGLYSS. Call your doctor for medical advice about side effects. You may report side effects to FDA at 1-800-FDA-1088.

How should I store EBGLYSS?

- Store EBGLYSS in the refrigerator between 36°F to 46°F (2°C to 8°C).
- EBGLYSS can be stored at room temperature up to 86°F (30°C) for up to 7 days in the original carton. Throw away (dispose of) EBGLYSS that has been left at room temperature for longer than 7 days.
- Store EBGLYSS in the original carton to protect from light until use.
- Do not freeze. Do not shake.
- Do not microwave EBGLYSS, or run hot water over it, or leave it in direct sunlight.

Keep EBGLYSS and all medicines out of the reach of children.

General information about the safe and effective use of EBGLYSS.
Medicines are sometimes prescribed for purposes other than those listed in a Patient Information leaflet. Do not use EBGLYSS for a condition for which it is not prescribed. Do not give EBGLYSS to other people, even if they have the same symptoms you have. It may harm them. You can ask your pharmacist of healthcare provider for information about EBGLYSS that is written for health professionals.

What are the ingredients in EBGLYSS?
Active ingredient: lebrikizumab-lbkz
Inactive ingredient: glacial acetic acid, histidine, polysorbate 20, sucrose, and Water for Injection.
EBGLYSS prefilled pen and prefilled syringe with needle shield are not made with natural rubber latex.

EBGLYSS is a trademark of Eli Lilly and Company.
Eli Lilly and Company, Indianapolis, IN 46285
US License Number 1891
Copyright © 2024, Eli Lilly and Company. All rights reserved.
For more information about EBGLYSS, call 1-800-545-5979 (1-800-Lilly-Rx) or go to www.ebglyss.com

This Patient Information has been approved by the U.S. Food and Drug Administration

Revised: 09/2024

EBG-0001-PPI-202409

PREFILLED PEN INSTRUCTIONS FOR USE

INSTRUCTIONS FOR USE

EBGLYSS™ [EHB-glihs]

(lebrikizumab-lbkz)

injection, for subcutaneous use

Single-Dose Prefilled Pen

This Instructions for Use contains information on how to inject EBGLYSS.

Before you use the EBGLYSS Prefilled Pen (Pen), read and carefully follow all the step-by-step instructions.

Important information you need to know before injecting EBGLYSS

- Your healthcare provider should show you how to prepare and inject EBGLYSS using the Pen. Do not inject yourself or someone else until you have been shown how to inject EBGLYSS.

- Keep this Instructions for Use and read it as needed.

- Each EBGLYSS Pen contains 1 dose of EBGLYSS. The Pen is for one-time use only.

- The EBGLYSS Pen contains glass parts. Handle it carefully. If you drop it on a hard surface, do not use it. Use a new EBGLYSS Pen for your injection.

- Your healthcare provider may help you decide where on your body to inject your dose. You can also read the Choose and clean your injection site section of these instructions to help you choose which area can work best for you.

- If you have vision or hearing problems, do not use EBGLYSS Pen without help from a caregiver.

- See Storing EBGLYSS for important storage information.

INSTRUCTIONS FOR USE

Before you use the EBGLYSS Pen, read and carefully follow all the step-by-step instructions.

Parts of the EBGLYSS Pen

Preparing to inject EBGLYSS

Gather supplies and EBGLYSS Pen:

- EBGLYSS Pen from the refrigerator
- 1 alcohol wipe

- 1 cotton ball or piece of gauze
- 1 sharps disposal container
  (See Disposing of EBGLYSS)

Note: You do not need to allow your Pen to warm up to room temperature before use.

Inspect the Pen and the medicine

Leave the gray base cap on until you are ready to inject. Make sure you have the right medicine. The medicine inside should be clear. It may be colorless to slightly yellow to slightly brown.

Do not use the Pen (see Disposing of EBGLYSS) if the:

- Pen looks damaged
- medicine is frozen
- medicine is cloudy, is discolored, or has particles
- expiration date printed on the label has passed

Wash your hands with soap and water

Choose and clean your injection site

Your healthcare provider can help you choose the injection site that is best for you.
Clean the injection site with an alcohol wipe and let dry.

You or another person may inject into these areas.

- Stomach area (abdomen) —
  At least 2 inches away from the belly button (navel).
- Front of thigh —
  At least 2 inches above the knee and 2 inches below the groin.

Another person should inject into this area.

- Back of upper arm —
  Another person should inject into the back of your upper arm.

Do not inject in the exact same spot every time.
Do not inject into areas where the skin is tender, bruised, red, hard, or in an area of skin that is affected by eczema (atopic dermatitis) or other skin lesions.

Injecting EBGLYSS
1 | Uncap the Pen
 |  |  |  |  |  | Make sure the Pen is locked.
 |  |  |  |  |  | When you are ready to inject, twist off the gray base cap and throw it away in your household trash. Do not put the gray base cap back on; this could damage the needle. Do not touch the needle inside the clear base.
2 | Place and unlock
 |  |  |  |  |  | Place and hold the clear base flat and firmly against the skin.
 |  |  |  |  |  | Keep the clear base on the skin, then turn the lock ring to the unlock position.
3 | Press and hold for 15 seconds
 |  |  | Press and hold the purple injection button and listen for 2 loud clicks:; - First click: injection started - Second click: injection completed; The injection may take up to 15 seconds.
 | You will know the injection is complete when the gray plunger is visible.
Disposing of EBGLYSS
Dispose of (throw away) the used Pen
 |  |  |  |  | Put the used EBGLYSS Pen in an FDA-cleared sharps disposal container right away after use.
Do not throw away (dispose of) the EBGLYSS Pen in your household trash.
If you do not have an FDA-cleared sharps disposal container, you may use a household container that is:
 | - made of a heavy-duty plastic,
 | - can be closed with a tight-fitting, puncture-resistant lid, without sharps being able to come out,
 | - upright and stable during use,
 | - leak-resistant, and
 | - properly labeled to warn of hazardous waste inside the container.
When your sharps disposal container is almost full, you will need to follow your community guidelines for the right way to dispose of your sharps disposal container.
There may be state or local laws about how you should throw away needles and syringes.
For more information about safe sharps disposal, and for specific information about sharps disposal in the state you live in, go to the FDA's website at: http://www.fda.gov/safesharpsdisposal.
Do not recycle your used sharps disposal container.
Commonly asked questions
Q. | What if I see air bubbles in the Pen?
A. | Air bubbles are normal. They will not harm you or affect your dose.
Q. | What if my Pen is not at room temperature?
A. | You do not need to allow your Pen to warm up to room temperature before injecting.
Q. | What if there is a drop of liquid on the tip of the needle when I remove the gray base cap?
A. | A drop of liquid on the tip of the needle is normal. This will not harm you or affect your dose.
Q. | What if I unlock the Pen and press the purple injection button before twisting off the gray base cap?
A. | Do not remove the gray base cap. Throw away (dispose of) the Pen and use a new one.
Q. | Do I need to hold the purple injection button down until the injection is complete?
A. | You do not need to hold the purple injection button down, but it may help you keep the Pen steady and firm against your skin.
Q. | What if the needle did not retract after my injection?
A. | Do not touch the needle or replace the gray base cap. Store the Pen in a safe place to avoid an accidental needlestick and contact Lilly at 1-800-Lilly-Rx (1-800-545-5979) for instructions on how to return the Pen.
Q. | What if there is a drop of liquid or blood on my skin after my injection?
A. | This is normal. Press a cotton ball or gauze over the injection site. Do not rub the injection site.
Q. | How can I tell if my injection is complete?
A. | After you press the purple injection button, you will hear 2 loud clicks. The second loud click tells you that your injection is complete. You will also see the gray plunger at the top of the clear base. The injection may take up to 15 seconds.
Q. | What if I remove the Prefilled Pen before the second loud click or before the gray plunger stops moving?
A. | You may not have received your full dose. Do not give another injection. Call your healthcare provider for help.
Q. | What if I heard more than 2 clicks during my injection, 2 loud clicks and 1 soft one. Did I get my complete injection?
A. | Some people may hear a soft click right before the second loud click. That is the normal operation of the Prefilled Pen. Do not remove the Prefilled Pen from your skin until you hear the second loud click.
If you have more questions about how to use the EBGLYSS Prefilled Pen:
 | - Call your healthcare provider |  |  |  |  |  | Scan this code to launch www.ebglyss.com
 | - Call 1-800-Lilly-Rx (1-800-545-5979) |  |  |  |  |  | Scan this code to launch www.ebglyss.com
 | - Visit www.ebglyss.com |  |  |  |  |  | Scan this code to launch www.ebglyss.com

Storing EBGLYSS

- Store your Pen in the refrigerator between 36ºF to 46ºF (2°C to 8°C).

- EBGLYSS can be stored at room temperature up to 7 days in the original carton. Do not store above 86°F (30°C). Throw away (dispose of) EBGLYSS that has been left at room temperature for longer than 7 days.

- Store your Pen in the original carton to protect from light until use.

- Do not freeze your Pen. Do not shake your Pen.

- Do not microwave your Pen, or run hot water over it, or leave it in direct sunlight.

- Throw away (dispose of) your Pen if any of the above conditions are not followed.

Keep your Pen and all medicines out of the reach of children.

Read the Patient Information insert for EBGLYSS inside this box to learn more about your medicine.

Eli Lilly and Company
Indianapolis, IN 46285, USA
US License Number 1891

EBGLYSS is a trademark of Eli Lilly and Company.
Copyright © 2024, Eli Lilly and Company. All rights reserved.

This Instructions for Use has been approved by the U.S. Food and Drug Administration.
Revised: MAY 2025
EBG-0003-PEN-IFU-20250521

PREFILLED SYRINGE INSTRUCTIONS FOR USE

INSTRUCTIONS FOR USE

EBGLYSS™ [EHB-glihs]

(lebrikizumab-lbkz)

injection, for subcutaneous use

Single-Dose Prefilled Syringe with Needle Shield

This Instructions for Use contains information on how to inject EBGLYSS.

Before you use the EBGLYSS Prefilled Syringe with Needle Shield (Prefilled Syringe), read and carefully follow all the step-by-step instructions.

Important information you need to know before injecting EBGLYSS

- Your healthcare provider should show you how to prepare and inject EBGLYSS using the Prefilled Syringe. Do not inject yourself or someone else until you have been shown how to inject EBGLYSS.
- Keep these Instructions for Use and read it as needed.
- Each EBGLYSS Prefilled Syringe contains 1 dose of EBGLYSS. The Prefilled Syringe is for one-time use only.
- The EBGLYSS Prefilled Syringe contains glass parts. Handle it carefully. If you drop it on a hard surface, do not use it. Use a new EBGLYSS Prefilled Syringe for your injection.
- Your healthcare provider may help you decide where on your body to inject your dose. You can also read the Choose and clean your injection site section of these instructions to help you choose which area can work best for you.
- If you have vision problems, do not use the EBGLYSS Prefilled Syringe without help from a caregiver.
- See Storing EBGLYSS for important storage information.

INSTRUCTIONS FOR USE

Before you use the EBGLYSS Prefilled Syringe, read and carefully follow all the step-by-step instructions.

Parts of the EBGLYSS Prefilled Syringe with Needle Shield

Preparing to inject EBGLYSS

Gather Supplies and EBGLYSS Prefilled Syringe

- EBGLYSS Prefilled Syringe from the refrigerator
- 1 alcohol wipe
- 1 cotton ball or piece of gauze
- 1 sharps disposal container (see Disposing of EBGLYSS)

Note: You do not need to allow your Prefilled Syringe to warm up to room temperature before use.

Remove Prefilled Syringe from carton

Remove the EBGLYSS Prefilled Syringe from the carton by holding the middle of the Syringe Body and then place the EBGLYSS Prefilled Syringe on a clean flat surface.
Leave the needle cap on the syringe until you are ready to inject.
Do not pull back on the Plunger Rod at any time.

Inspect the Prefilled Syringe and the medicine
Make sure you have the right medicine. The medicine inside should be clear. It may be colorless to slightly yellow to slightly brown. Some air bubbles are normal.

Note: You may gently rotate the plunger rod to view the syringe label if needed.
Do not use the Prefilled Syringe (see Disposing of EBGLYSS) if the:

- Needle Cap is missing or not securely attached
- Prefilled Syringe looks damaged
- medicine is frozen
- medicine is cloudy, is discolored, or has particles
- expiration date printed on the label has passed.

Wash your hands with soap and water

Choose and clean your injection site
Your healthcare provider can help you choose the injection site that is best for you. Clean the injection site with an alcohol wipe and let dry.

You or another person may inject into these areas.

- Stomach area (abdomen) –
  - At least 2 inches away from the belly button (navel).
- Front of thigh –
  - At least 2 inches above the knee and 2 inches below the groin.

Another person should inject into this area.

- Back of upper arm –
  - Another person should inject into the back of your upper arm.
  Do not inject in the exact same spot every time.
  Do not inject into areas where the skin is tender, bruised, red, hard, or in an area of the skin that is affected by eczema (atopic dermatitis) or other skin lesions.

Injecting EBGLYSS
1 | Remove Needle Cap
1 |  | Hold the EBGLYSS Prefilled Syringe in the middle of the Syringe Body and pull the Needle Cap straight off. Do not put the Needle Cap back on; this could damage the needle. Do not touch the Needle.
2 | Pinch the injection site and insert the Needle
 |  | Gently pinch a fold of skin at the injection site with one hand. Insert the Needle completely into the fold of skin at about a 45º angle with your other hand.
3 | Push in the Plunger Rod
3 |  | Gently relax the pinch while keeping the needle in place. Push the Plunger Rod all the way down as far as it will go to inject all of the medicine. Note: It is normal to feel some resistance. You have to give the full dose to activate the Needle Shield.
4 | Release the Plunger Rod
 |  | Lift your thumb to release the Plunger Rod until the Needle is covered by the Needle Shield. Lightly press a cotton ball or gauze on the injection site if you see any blood. Do not rub your skin after the injection.

Disposing of EBGLYSS

Dispose of (throw away) the used Prefilled Syringe

Put the used EBGLYSS Prefilled Syringe and Needle Cap in an FDA-cleared sharps disposal container right away after use.

Do not throw away (dispose of) the EBGLYSS Prefilled Syringe in your household trash.
If you do not have an FDA-cleared sharps disposal container, you may use a household container that is:

- made of a heavy-duty plastic,
- able to be closed with a tight-fitting, puncture-resistant lid, without sharps being able to come out,
- upright and stable during use,
- leak-resistant, and
- properly labeled to warn of hazardous waste inside the container.

When your sharps disposal container is almost full, you will need to follow your community guidelines for the right way to dispose of your sharps disposal container.
There may be local laws about how you should throw away needles and syringes.
For more information about safe sharps disposal, and for specific information about sharps disposal in the state you live in, go to the FDA website at: http://www.fda.gov/safesharpsdisposal
Do not recycle your used sharps disposal container.

Storing EBGLYSS

- Store your Prefilled Syringe in a refrigerator between 36°F to 46°F (2°C to 8°C).
- EBGLYSS can be stored at room temperature up to 7 days in the original carton. Do not store above 86°F (30°C). Throw away (dispose of) EBGLYSS that has been left at room temperature for longer than 7 days.
- Store your Prefilled Syringe in the original carton to protect from light until use.
- Do not freeze your Prefilled Syringe. Do not shake your Prefilled Syringe.
- Do not microwave your Prefilled Syringe, or run hot water over it, or leave it in direct sunlight.
- Throw away (dispose of) your Prefilled Syringe if any of the above conditions are not followed.

Keep your Prefilled Syringes and all medicines out of the reach of children.

If you have more questions about how to use the EBGLYSS Prefilled Syringe:
- Call your healthcare provider |  | Scan this code to launch www.ebglyss.com
- Call 1-800-Lilly-Rx (1-800-545-5979) |  | Scan this code to launch www.ebglyss.com
- Visit www.ebglyss.com |  | Scan this code to launch www.ebglyss.com

Read the Patient Information insert for EBGLYSS inside this box to learn more about your medicine.

Eli Lilly and Company

Indianapolis, IN 46285, USA

US License Number 1891

EBGLYSS is a trademark of Eli Lilly and Company.

Copyright © 2024, 2025, Eli Lilly and Company. All rights reserved.

This Instructions for Use has been approved by the U.S. Food and Drug Administration.

Revised: October 2025

EBG-0002-PFS-IFU-20251028

PACKAGE LABEL – Ebglyss 250 mg Prefilled Pen

Ebglyss®

(lebrikizumab-lbkz)
injection

250 mg / 2 mL

1 Single-Dose Prefilled Pen

NDC 0002-7772-11

1 x 250 mg/2 mL
Single-Dose Prefilled Pen

For Subcutaneous Use Only

Rx only

Lilly

PACKAGE LABEL – Ebglyss 250 mg Prefilled Syringe

Ebglyss ®

(lebrikizumab-lbkz)
injection

250 mg / 2 mL

1 Single-Dose Prefilled Syringe with Needle Shield

NDC 0002-7797-11

1 x 250 mg/2 mL
(125 mg/mL)
Single-Dose Prefilled Syringe with Needle Shield

For Subcutaneous Use Only

Rx only

Lilly